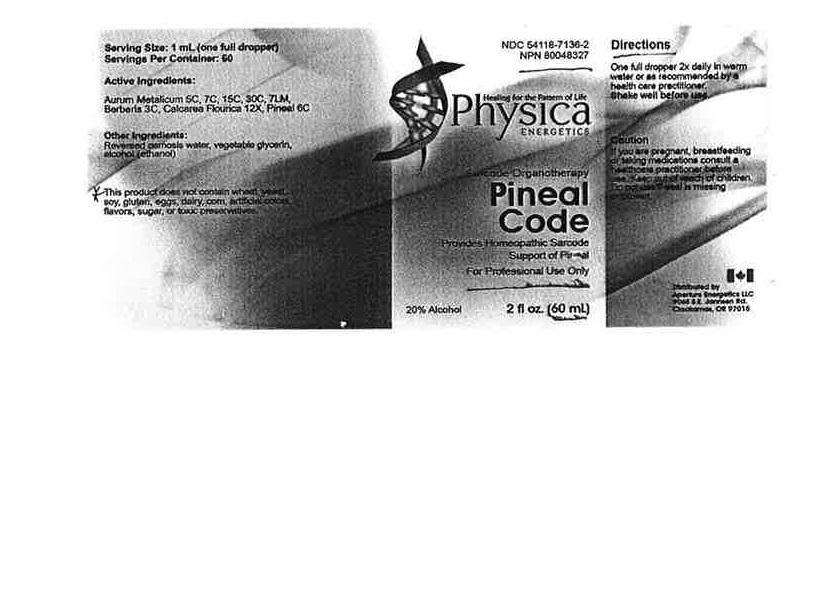 DRUG LABEL: Pineal Code
NDC: 54118-7136 | Form: SOLUTION/ DROPS
Manufacturer: ABCO Labratories, Inc.
Category: homeopathic | Type: HUMAN OTC DRUG LABEL
Date: 20150717

ACTIVE INGREDIENTS: BOS TAURUS PINEAL GLAND 6 [hp_C]/60 mL; GOLD 5 [hp_C]/60 mL; BERBERIS VULGARIS FRUIT 3 [hp_C]/60 mL; CALCIUM FLUORIDE 12 [hp_X]/60 mL
INACTIVE INGREDIENTS: WATER; ALCOHOL; GLYCERIN

Pineal Code

WARNINGS

- If you are pregnant, breasfeeding or taking medications consult a healthcare practitioner before use.
- Keep out of reach of children.
- Do not use if seal is missing or broken.

KEEP OUT OF REACH OF CHILDREN!

PURPOSE

Provides Homeopathic Sarcode Support of Pineal.

DOSAGE AND ADMINISTRATION

- One full dropper 2x daily in warm water or as recommended by a heal care practitioner.
- Shake well before use.

INDICATIONS AND USAGE

Sarcode Organotherapy.

INACTIVE INGREDIENT

Reversed osmosis water, vegetable glycerin, alcohol (ethanol).

ACTIVE INGREDIENT

Aurum Metallicum 5CH, 7CH, 15CH, 30CH, 7MH, Berberis 3CH, Calcarea Flourica 12X, Pineal 6CH.